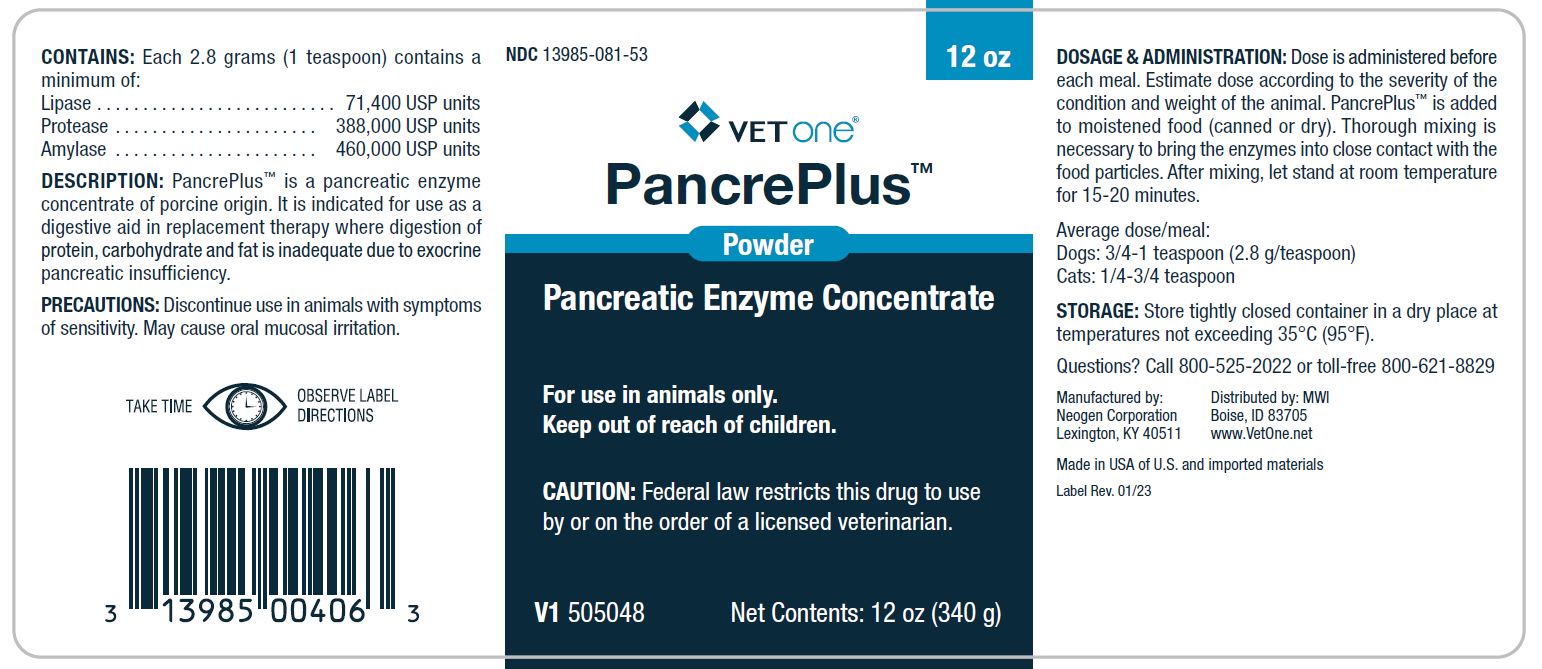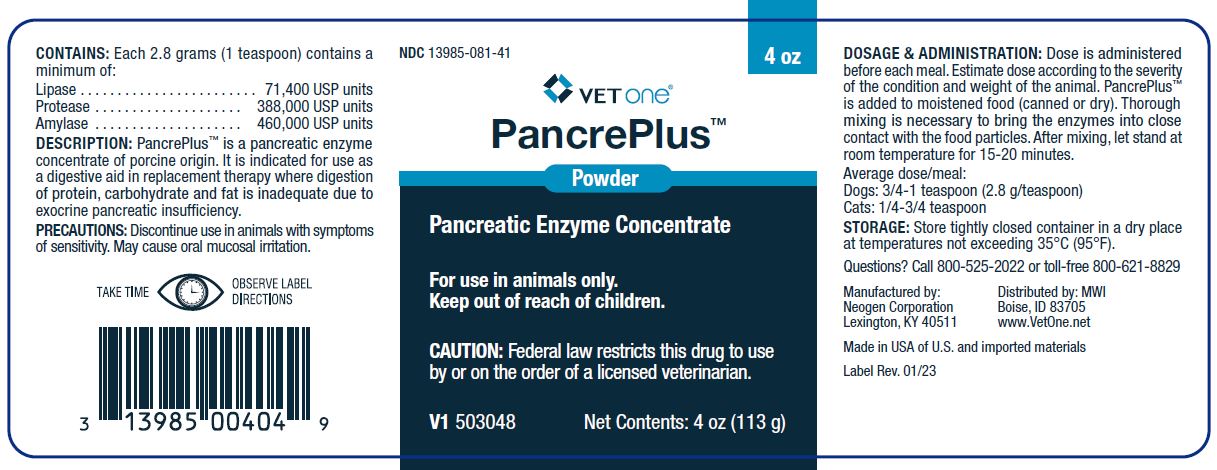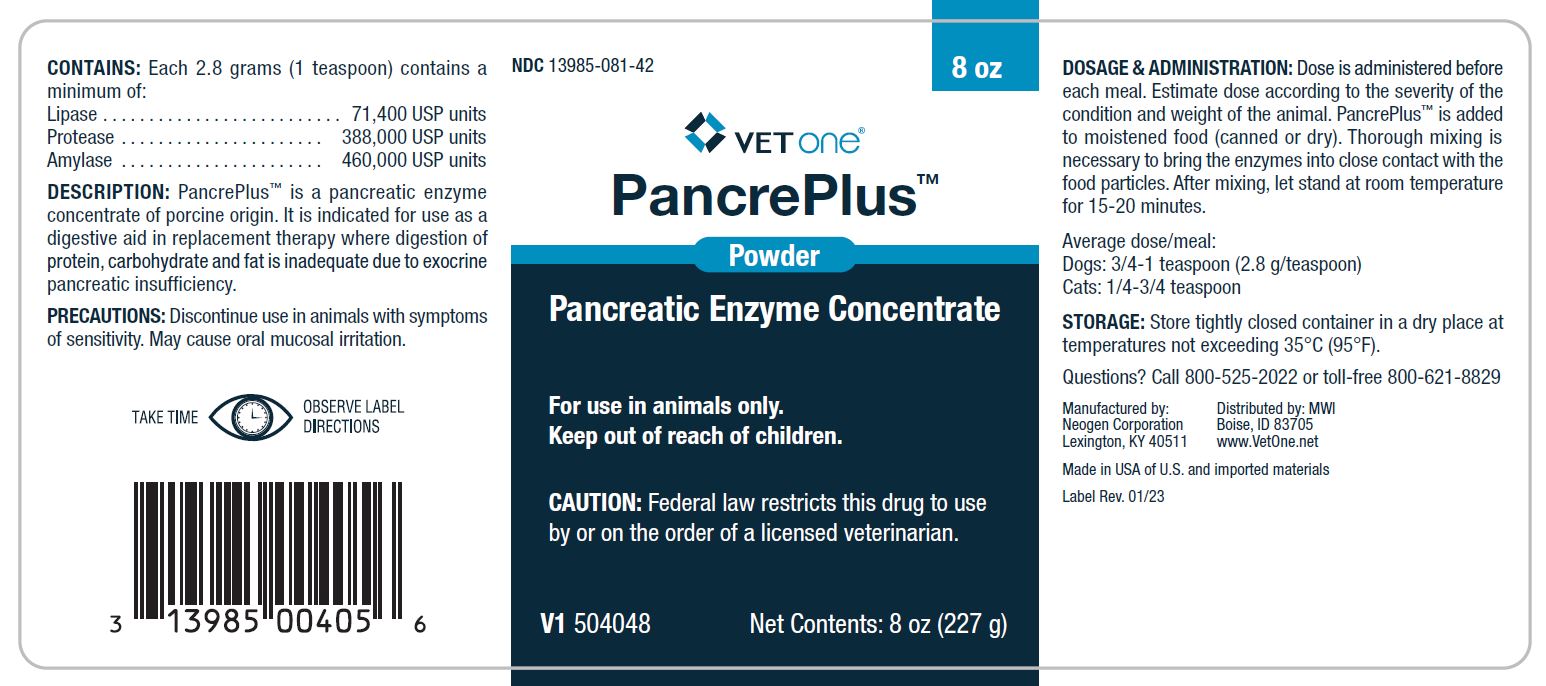 DRUG LABEL: PancrePlus
NDC: 13985-081 | Form: Powder
Manufacturer: MWI/VetOne
Category: animal | Type: PRESCRIPTION ANIMAL DRUG LABEL
Date: 20240510

ACTIVE INGREDIENTS: PANCRELIPASE LIPASE 71400 [iU]/2.8 g; PANCRELIPASE AMYLASE 460000 [iU]/2.8 g; PANCRELIPASE PROTEASE 388000 [iU]/2.8 g

CONTAINS:

Each 2.8 grams (1 teaspoon) contains a minimum of:

Lipase..............................71,400 USP units

Protease.........................388,000 USP units

Amylase..........................460,000 USP unitsC

DESCRIPTION:

PancrePlus™ is a pancreatic enzyme concentrate of porcine origin.

INDICATIONS AND USAGE

It is indicated for use as a digestive aid in replacement therapy where digestion of protein, carbohydrate and fat is inadequate due to exocrine pancreatic insufficiency.

PRECAUTIONS:

Discontinue use in animals with symptoms of sensitivity. May cause oral mucosal irritation.

Questions? Call 800-525-2022 or toll-free 800-621-8829

DOSAGE & ADMINISTRATION:

Dose is administered before each meal. Estimate dose according to the severity of the condition and weight of the animal. PanaKare Plus is added to moistened food (canned or dry). Thorough mixing is necessary to bring the enzymes into close contact with the food particles. After mixing, let stand at room temperature for 15-20 minutes.

Average dose/meal:

Dogs: 3/4-1 teaspoon (2.8g/teaspoon)

Cats: 1/4-3/4 teaspoon

STORAGE:

Store tightly closed container in a dry place at temperatures not exceeding 35°C (95°F).

PRINCIPAL DISPLAY PANEL - 4 oz Bottle

NDC 13985-081-41 4 oz

VETone®

PancrePlus™

Powder

Pancreatic Enzyme Concentrate

For use in animals only.

Keep out of reach of children.

CAUTION: Federal law restricts this drug to use by or on the order of a licensed veterinarian.

V1 503048 Net Contents:4 oz (113 g)

PRINCIPAL DISPLAY PANEL - 8 oz Bottle

NDC 13985-081-42 8 oz

VETone®

PancrePlus™

Powder

Pancreatic Enzyme Concentrate

For use in animals only.

Keep out of reach of children.

CAUTION: Federal law restricts this drug to use by or on the order of a licensed veterinarian.

V1 504048 Net Contents: 8 oz (227 g)

PRINCIPAL DISPLAY PANEL - 12 oz Bottle

NDC 13985-081-53 12 oz

VETone®

PancrePlus™

Powder

Pancreatic Enzyme Concentrate

For use in animals only.

Keep out of reach of children.

CAUTION: Federal law restricts this drug to use by or on the order of a licensed veterinarian.

V1 505048 Net Contents: 12 oz (340 g)